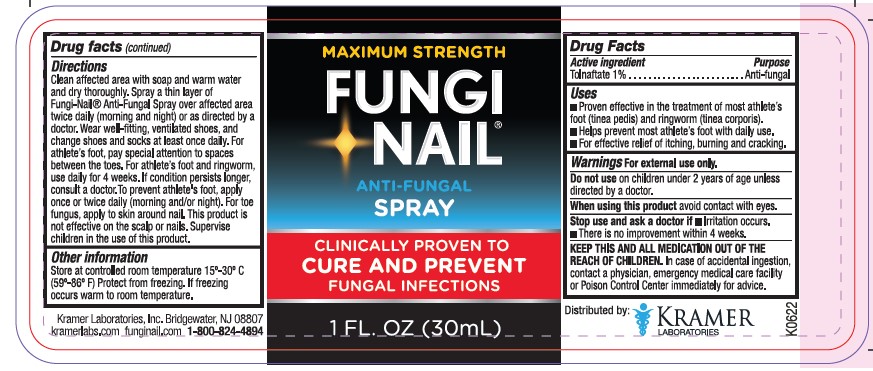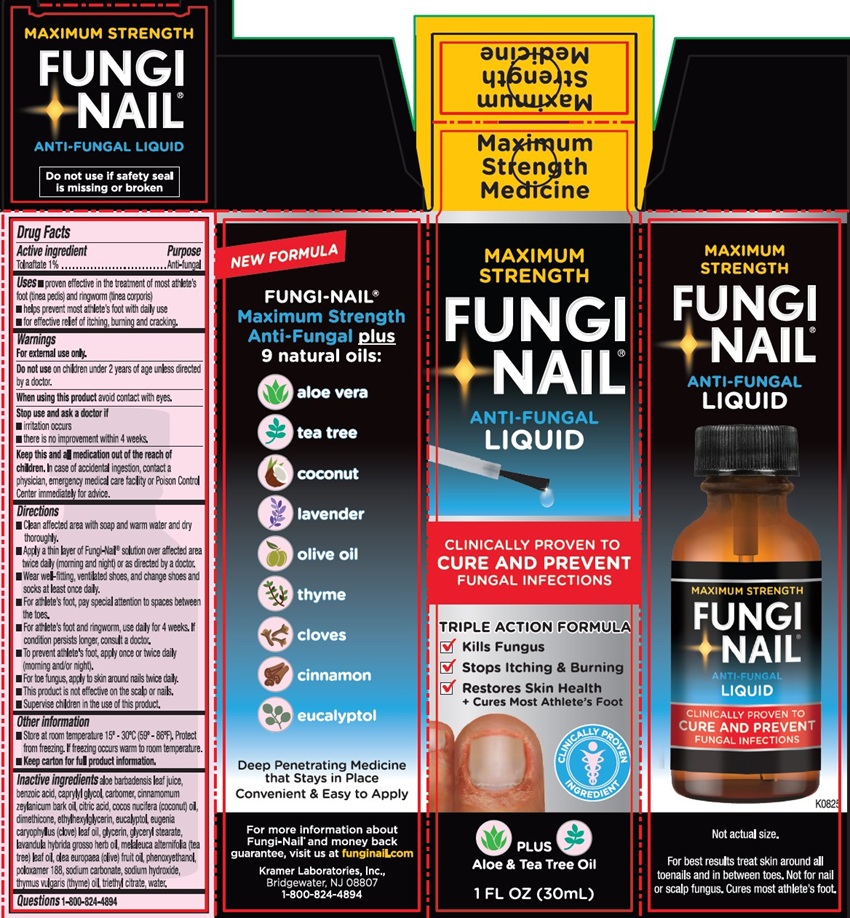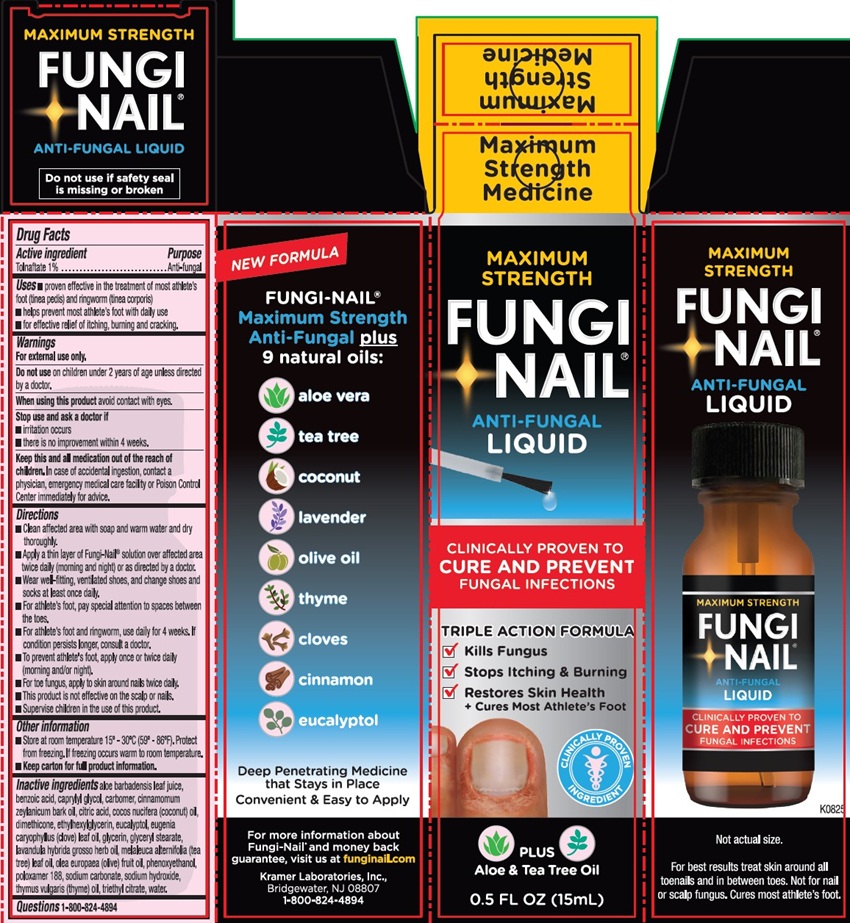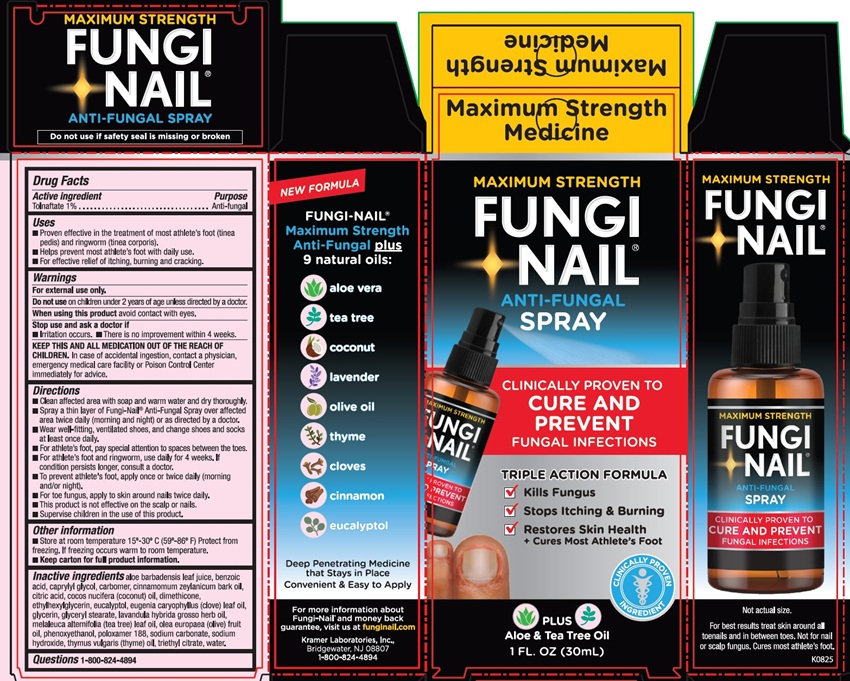 DRUG LABEL: Fungi Nail Toe and Foot
NDC: 55505-177 | Form: SOLUTION
Manufacturer: Kramer Laboratories
Category: otc | Type: HUMAN OTC DRUG LABEL
Date: 20251219

ACTIVE INGREDIENTS: Tolnaftate 10 mg/1 mL
INACTIVE INGREDIENTS: Aloe Vera Leaf; Benzoic Acid; Caprylyl Glycol; Carbomer Homopolymer Type A (Allyl Pentaerythritol Crosslinked); Cinnamomum Massoy Bark Oil; Citric Acid Monohydrate; Cocos Nucifera Whole; Dimethicone 350; Ethylhexylglycerin; Eucalyptol; Eugenia Uniflora Leaf; Glycerin; Glyceryl Monostearate; Lavender Oil; Tea Tree Oil; Olive Oil; Phenoxyethanol; Poloxamer 188; Sodium Carbonate; Sodium Hydroxide; Thyme; Triethyl Citrate; Water

Drug Facts

ACTIVE INGREDIENT

Active Ingredient | Purpose
Tolnaftate 1% | Anti-fungal

INDICATIONS AND USAGE

Uses ■ Proven effective in the treatment of most athlete’s foot (tinea pedis) and ringworm (tinea corporis) ■ Helps prevent most athlete's foot with daily use ■ For effective relief of itching, burning and cracking.

Warnings

For external use only.

Do not use on children under 2 years of age unless directed by a doctor.

When using this product avoid contact with eyes.

Stop use and ask a doctor if ■ irritation occurs ■ there is no improvement within 4 weeks.

KEEP OUT OF REACH OF CHILDREN

Keep this and all medication out of the reach of children. In case of accidental ingestion, contact a physician, emergency medical care facility or Poison Control Center immediately for advice.

Directions:
■ Clean affected areas with soap and warm water and dry thoroughly. ■ Apply a thin layer of Fungi-Nail® Anti-Fungal Liquid over affected area twice daily (morning and night) or as directed by a doctor. ■ Wear well-fitting, ventilated shoes, and change shoes and socks at least once daily. ■ For athlete’s foot pay special attention to spaces between the toes. ■ For athlete’s foot and ringworm, use daily for 4 weeks. If condition persists longer, consult a doctor. ■ To prevent athlete's foot, apply once or twice daily (morning and/or night). ■ This product is not effective on the scalp or nails. ■ Supervise children in the use of this product.

Other information
■ Store at room temperature 15°-30°C (59°-86°F). Protect from freezing. If freezing occurs warm to room temperature. ■ Keep carton for full product information.

INACTIVE INGREDIENT

Inactive ingredients aloe barbadensis leaf juice, benzoic acid, caprylyl glycol, carbomer, cinnamomum zeylanicum bark oil, citric acid, cocos nucifera (coconut) oil, dimethicone, ethylhexylglycerin, eucalyptol, eugenia caryophyllus (clove) leaf oil, glycerin, glyceryl stearate, lavandula hybrida grosso herb oil, melaleuca alternifolia (tea tree) leaf oil, olea europaea (olive) fruit oil, phenoxyethanol, poloxamer 188, sodium carbonate, sodium hydroxide, thymus vulgaris (thyme) oil, triethyl citrate, water.

PRINCIPAL DISPLAY PANEL

MAXIMUM
STRENGTH
FUNGI-NAIL®
ANTI-FUNGAL
LIQUID
CLINICALLY PROVEN TO
CURE AND PREVENT
FUNGAL INFECTIONS
TRIPLE ACTION FORMULA
✓ Kills Fungus
✓ Stops Itching & Burning
✓ Restores Skin Health
* Cures Most Athlete's Foot
CLINICALLY PROVEN INGREDIENT
PLUS
Aloe & Tea Tree Oil
1 FL. OZ. (30mL)
NEW FORMULA
FUNGI-NAIL®
Maximum Strength
Anti-Fungal plus
9 natural oils:
○ aloe vera
○ tea tree
○ coconut
○ lavender
○ olive oil
○ thyme
○ cloves
○ cinnamon
○ eucalyptol
Deep Penetrating Medicine
that Stays in Place
Convenient & Easy to Apply
For more information about
Fungi-Nail® and money back
guarantee, visit us at funginail.com
Kramer Laboratories, Inc.
Bridgewater, NJ 08807
1-800-824-4894
K0825
Not actual size.
For best results treat skin around all
toenails and in between toes. Not for nail
or scalp fungus. Cures most athlete's foot.
Do not use if safety seal
is missing or broken

MAXIMUM
STRENGTH
FUNGI-NAIL®
ANTI-FUNGAL
SPRAY
CLINICALLY PROVEN TO
CURE AND
PREVENT
FUNGAL INFECTIONS
TRIPLE ACTION FORMULA
✓ Kills Fungus
✓ Stops Itching & Burning
✓ Restores Skin Health
* Cures Most Athlete's Foot
CLINICALLY PROVEN INGREDIENT
PLUS
Aloe & Tea Tree Oil
1 FL. OZ. (30mL)
NEW FORMULA
FUNGI-NAIL®
Maximum Strength
Anti-Fungal plus
9 natural oils:
○ aloe vera
○ tea tree
○ coconut
○ lavender
○ olive oil
○ thyme
○ cloves
○ cinnamon
○ eucalyptol
Deep Penetrating Medicine
that Stays in Place
Convenient & Easy to Apply
For more information about
Fungi-Nail® and money back
guarantee, visit us at funginail.com
Kramer Laboratories, Inc.
Bridgewater, NJ 08807
1-800-824-4894
K0825
Not actual size.
For best results treat skin around all
toenails and in between toes. Not for nail
or scalp fungus. Cures most athlete's foot.
Do not use if safety seal is missing or broken

MAXIMUM STRENGTH
FUNGI-NAIL®
ANTI-FUNGAL
SPRAY
CLINICALLY PROVEN TO
CURE AND PREVENT
FUNGAL INFECTIONS
1 FL OZ (30mL)
Distributed by:
KRAMER
LABORITORIES
K0622
Kramer Laboratories, Inc. Bridgewater, NJ 08807
kramerlabs.com funginal.com 1-800-824-4894

MAXIMUM
STRENGTH
FUNGI
-NAIL®
ANTI-FUNGAL
LIQUID
CLINICALLY PROVEN TO
CURE AND PREVENT
FUNGAL INFECTIONS
TRIPLE ACTION FORMULA
✓ Kills Fungus
✓ Stops Itching & Burning
✓ Restores Skin Health
* Cures Most Athlete's Foot
CLINICALLY PROVEN INGREDIENT
PLUS
Aloe & Tea Tree Oil
0.5 FL. OZ. (15mL)
NEW FORMULA
FUNGI-NAIL®
Maximum Strength
Anti-Fungal plus
9 natural oils:
○ aloe vera
○ tea tree
○ coconut
○ lavender
○ olive oil
○ thyme
○ cloves
○ cinnamon
○ eucalyptol
Deep Penetrating Medicine
that Stays in Place
Convenient & Easy to Apply
For more information about
Fungi-Nail® and money back
guarantee, visit us at funginail.com
Kramer Laboratories, Inc.
Bridgewater, NJ 08807
1-800-824-4894
K0825
Not actual size.
For best results treat skin around all
toenails and in between toes. Not for nail
or scalp fungus. Cures most athlete's foot.
Do not use if safety seal
is missing or broken